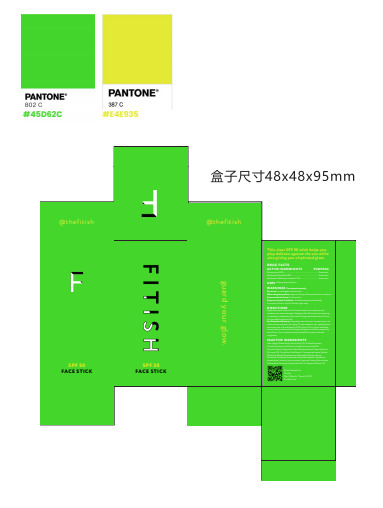 DRUG LABEL: FITISH SPF 50 FACE
NDC: 84417-002 | Form: STICK
Manufacturer: Fitish Holdings, LLC
Category: otc | Type: HUMAN OTC DRUG LABEL
Date: 20240815

ACTIVE INGREDIENTS: OCTINOXATE 7.5 g/100 g; OCTOCRYLENE 8 g/100 g; OCTISALATE 5 g/100 g
INACTIVE INGREDIENTS: DEXTRIN PALMITATE (CORN; 20000 MW); ALKYL (C12-15) BENZOATE; GREEN TEA LEAF; TEA LEAF OIL; MEDIUM-CHAIN TRIGLYCERIDES; CETYL ETHYLHEXANOATE; COCONUT; CYCLOMETHICONE 5; ETHYL MACADAMIATE; 2-ETHYLHEXYL ISOHEXADECANOATE; DIBUTYL LAUROYL GLUTAMIDE; DIBUTYL ETHYLHEXANOYL GLUTAMIDE; DICAPRYLYL CARBONATE; JOJOBA OIL

84417-002

Active Ingredient(s)

Octocrylene 8.0% Ethylhexyl Salicylate 5.0% Ethylhexyl Methoxycinnamate 7.5 %

Purpose

Sunscreen

Use

USES Helps prevent sunburn

Warnings

WARNINGS For external use only.

Do not use on damaged or broken skin.

When using this product, keep out of eyes. Rinse with water to remove.

Stop use and ask doctorif rash occurs.

Keep out of reach of children. If swallowed, get medical help or contact a Poison Control Center right away.

Directions

Apply directly to clean skin 15 minutes before sun exposure and anywhere you want extra glow. Reapply after

40 minutes of swimming or sweating, immediately after towel drying and at least every 2 hours. Can be used

on body as well.

Sun Protection Measures Spending time in the sun increases your risk of skin cancer and early skin aging.

To decrease this risk, regularly use a sunscreen with a Broad Spectrum SPF value of 15 or higher and other

sun protection measures including limiting time in the sun, especially from 10 a.m.-2 p.m. and wear long-sleeved

shirts, pants, hats and sunglasses

Other information

No data available

Inactive ingredients

Aloe Yohjyu Matsu Ekisu (Aloe Vera), C12-15 Alkyl Benzoate, Camellia Sinensis Leaf Extract, Camellia Sinensis Leaf Oil, Caprylic/Capric Triglyceride, Cetyl Ethylhexanoate, Cocos Nucifera
(Coconut) Oil, Cocos Nucifera Extract, Cyclopentasiloxane, Dextrin Palmitate, Dibutyl Ethylhexanoyl Glutamide, Dibutyl Lauroyl Glutamide, Dicaprylyl Carbonate, Ethyl Macadamiate, Ethylhexyl
Isopalmitate, Isononyl Isononanoate, Isopropyl Lauroyl Sarcosinate, Simmondsia Chinensis (Jojoba) Seed Oil, Tocopherol (Vitamin E)